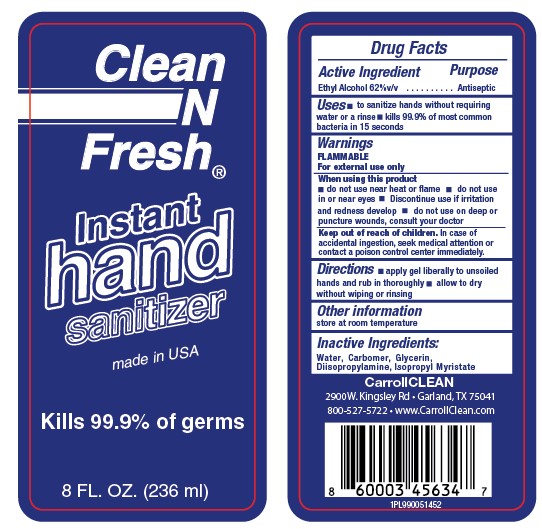 DRUG LABEL: Clean N Fresh Instant Hand Sanitizer Antibacterial
NDC: 73708-514 | Form: GEL
Manufacturer: CarrollClean, LLC
Category: otc | Type: HUMAN OTC DRUG LABEL
Date: 20200327

ACTIVE INGREDIENTS: ALCOHOL 147 mL/236 mL
INACTIVE INGREDIENTS: ISOPROPYL MYRISTATE 0.23 mL/236 mL; WATER 87.17 mL/236 mL; CARBOMER INTERPOLYMER TYPE A (55000 CPS) 0.75 mL/236 mL; DIISOPROPYLAMINE 0.39 mL/236 mL; GLYCERIN 0.45 mL/236 mL

Clean N Fresh® Instant Hand Sanitizer Antibacterial

PURPOSE

Antimicrobial

ACTIVE INGREDIENT

Ethyl Alcohol 62% v/v

USES

■ to sanitize hands without requiring water or a rinse

■ kills 99.9% of most common bacteria in 15 seconds

WARNINGS

FLAMMABLE

For External Use Only

WHEN USING THIS PRODUCT

■ do not use near heat or flame

■ do not use in or near eyes

■ discontinue use if irritation and redness develop

■ do not use on deep or puncture wounds, consult your doctor

KEEP OUT OF REACH OF CHILDREN

In case of accidental ingestion, seek medical attention or contact a poison control center immediately.

DIRECTIONS

■ apply gel liberally to unsoiled hands and run in thoroughly

■ allow to dry without washing or rinsing

OTHER INFORMATION

Store at room temperature

INACTIVE INGREDIENTS

Water, Carbomer, Diisopropylamine, Glycerin, Isopropyl Myristate